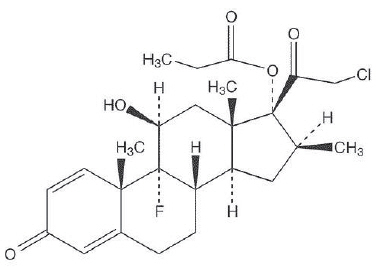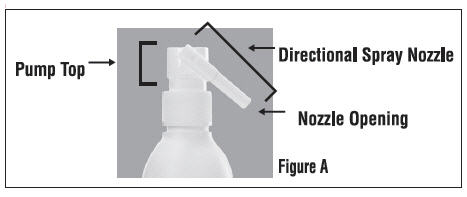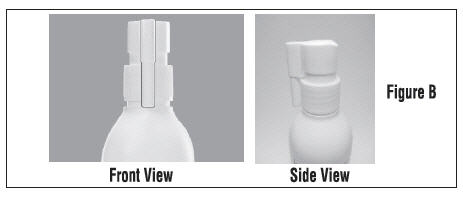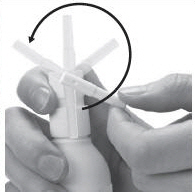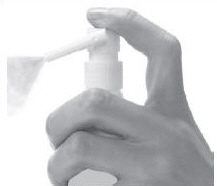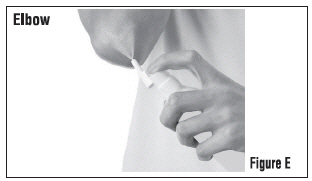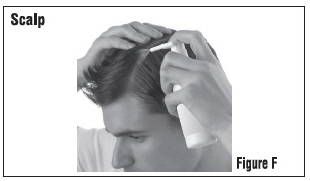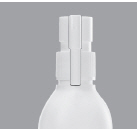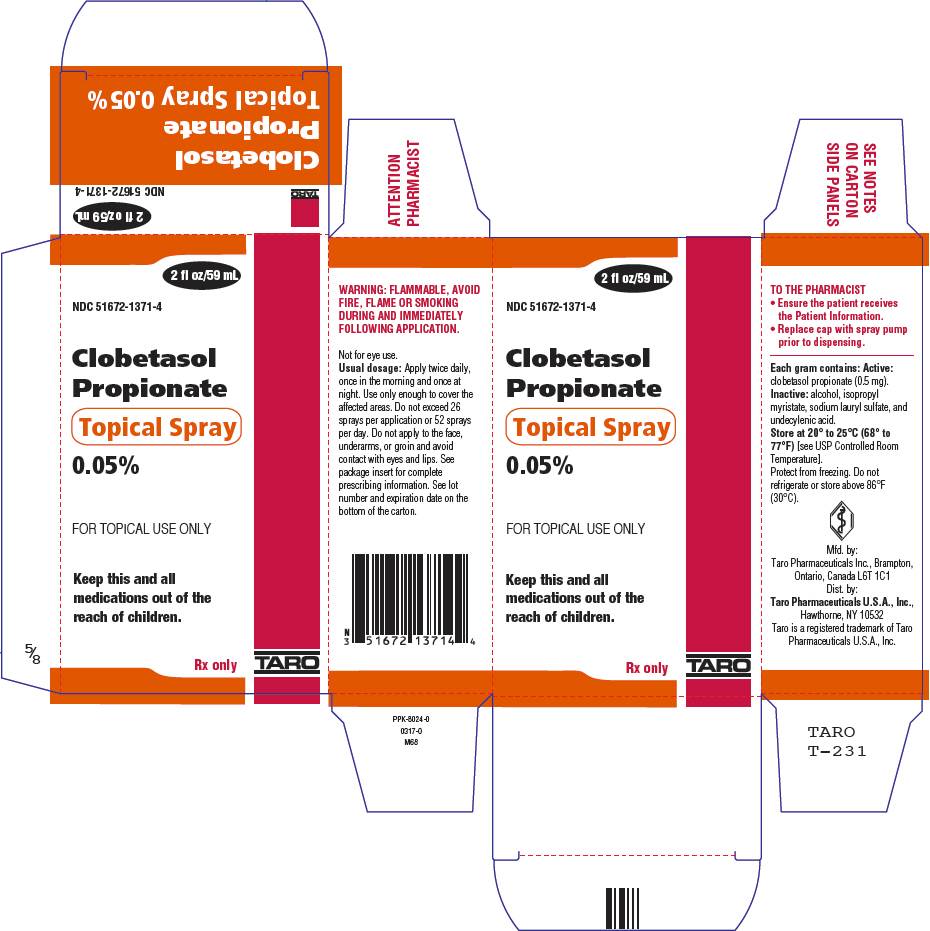 DRUG LABEL: Clobetasol Propionate
NDC: 51672-1371 | Form: SPRAY
Manufacturer: Sun Pharmaceutical Industries, Inc.
Category: prescription | Type: HUMAN PRESCRIPTION DRUG LABEL
Date: 20250703

ACTIVE INGREDIENTS: CLOBETASOL PROPIONATE 0.05 g/1 mL
INACTIVE INGREDIENTS: ALCOHOL; ISOPROPYL MYRISTATE; SODIUM LAURYL SULFATE; UNDECYLENIC ACID

HIGHLIGHTS OF PRESCRIBING INFORMATION

These highlights do not include all the information needed to use CLOBETASOL PROPIONATE TOPICAL SPRAY, 0.05% safely and effectively. See full prescribing information for CLOBETASOL PROPIONATE TOPICAL SPRAY, 0.05%.
CLOBETASOL PROPIONATE spray, 0.05%, for topical use
Initial U.S. Approval: 1985

1. INDICATIONS AND USAGE

Clobetasol Propionate Topical Spray, 0.05% is a corticosteroid indicated for the topical treatment of moderate to severe plaque psoriasis affecting up to 20% body surface area (BSA) in patients 18 years of age or older. (1.1)

Limitations of Use:

- Do not use on the face, axillae or groin. (1.2)
- Do not use if atrophy is present at the treatment site.(1.2)
- Do not use for rosacea or perioral dermatitis. (1.2)

2. DOSAGE AND ADMINISTRATION

- Not for oral, ophthalmic, or intravaginal use. (1.2)
- Clobetasol Propionate Topical Spray, 0.05% should be sprayed directly onto the affected skin areas twice daily and rubbed in gently. (2)
- The total dosage should not exceed 50 g (59 mL or 2 fluid ounces) per week. Do not use more than 26 sprays per application or 52 sprays per day. (2)
- Clobetasol Propionate Topical Spray, 0.05% contains a super-high potent topical corticosteroid; therefore treatment should be limited to 4 weeks.
- Treatment beyond 2 weeks should be limited to localized lesions of moderate to severe plaque psoriasis that have not sufficiently improved after the initial 2 weeks of treatment with Clobetasol Propionate Topical Spray, 0.05%. (2)

3. DOSAGE FORMS AND STRENGTHS

Spray, 0.05% w/w (3)

4. CONTRAINDICATIONS

None.

5. WARNINGS AND PRECAUTIONS

Clobetasol propionate is a highly potent topical corticosteroid that has been shown to suppress the HPA axis at the lowest doses tested. (5.1)

Cushing's syndrome, hyperglycemia, and unmasking of latent diabetes mellitus can also result from systemic absorption of topical corticosteroids. (5.1)

Systemic absorption may require periodic evaluation for HPA axis suppression. Modify use if HPA axis suppression develops. (5.1)

Children may be more susceptible to systemic toxicity from use of topical corticosteroids. (5.1, 8.4)

Local adverse reactions with topical corticosteroids may occur more frequently with the use of occlusive dressings and higher potency corticosteroids, including clobetasol propionate. These reactions include: folliculitis, acneiform eruptions, hypopigmentation, perioral dermatitis, allergic contact dermatitis, secondary infection, striae and miliaria. (5.2)

Clobetasol Propionate Topical Spray, 0.05% is flammable, keep away from heat or flame. (5.5)

6. ADVERSE REACTIONS

In controlled, clinical trials with Clobetasol Propionate Topical Spray, 0.05%, the most common adverse reactions (incidence > 2%) were burning, pruritus, nasopharyngitis, upper respiratory tract infection. (6.1)

To report SUSPECTED ADVERSE REACTIONS, contact Taro at 1-866-923-4914 or FDA at 1-800-FDA-1088 or www.fda.gov/medwatch.

FULL PRESCRIBING INFORMATION

1. INDICATIONS AND USAGE

1.1 Indication

Clobetasol Propionate Topical Spray, 0.05% is a super-high potent topical corticosteroid formulation indicated for the treatment of moderate to severe plaque psoriasis affecting up to 20% body surface area (BSA) in patients 18 years of age or older. The total dosage should not exceed 50 g (59 mL or 2 fl. oz.) per week. Do not use more than 26 sprays per application or 52 sprays per day. Treatment should be limited to 4 consecutive weeks.

Patients should be instructed to use Clobetasol Propionate Topical Spray, 0.05% for the minimum amount of time necessary to achieve the desired results [ see Dosage and Administration (2)].

Use in patients under 18 years of age is not recommended because safety has not been established and because numerically high rates of HPA axis suppression were seen with other clobetasol propionate topical formulations.

1.2 Limitations of Use

Clobetasol Propionate Topical Spray, 0.05% should not be used on the face, axillae, or groin. Clobetasol Propionate Topical Spray, 0.05% should not be used if there is atrophy at the treatment site. Clobetasol Propionate Topical Spray, 0.05% should not be used in the treatment of rosacea or perioral dermatitis.

2. DOSAGE AND ADMINISTRATION

Clobetasol Propionate Topical Spray, 0.05% is for topical use only, and not for ophthalmic, oral or intravaginal use.

Clobetasol Propionate Topical Spray, 0.05% should be sprayed directly onto the affected skin areas twice daily and rubbed in gently and completely.

The total dosage should not exceed 50 g (59 mL or 2 fluid ounces) per week because of the potential for the drug to suppress the hypothalamic-pituitary-adrenal (HPA) axis. Do not use more than 26 sprays per application or 52 sprays per day.

Clobetasol Propionate Topical Spray, 0.05% contains a topical corticosteroid; therefore treatment should be limited to 4 weeks. Therapy should be discontinued when control has been achieved. Treatment beyond 2 weeks should be limited to localized lesions of moderate to severe plaque psoriasis that have not sufficiently improved after the initial 2 weeks of treatment with Clobetasol Propionate Topical Spray, 0.05%. If no improvement is seen within 2 weeks, reassessment of diagnosis may be necessary. Before prescribing for more than 2 weeks, any additional benefits of extending treatment to 4 weeks should be weighed against the risk of HPA axis suppression. Use in pediatric patients younger than 18 years is not recommended because of the potential for HPA axis suppression [ see Use in Specific Populations (8.4)].

Unless directed by physician, Clobetasol Propionate Topical Spray, 0.05% should not be used with occlusive dressings.

3. DOSAGE FORMS AND STRENGTHS

Spray, 0.05% w/w. Each gram of Clobetasol Propionate Topical Spray, 0.05% contains 0.5 mg of clobetasol propionate in a clear, colorless liquid.

4. CONTRAINDICATIONS

None.

5. WARNINGS AND PRECAUTIONS

5.1 Effects on the Endocrine System

Clobetasol propionate is a highly potent topical corticosteroid that has been shown to suppress the HPA axis at the lowest doses tested. Systemic absorption of topical corticosteroids can produce reversible hypothalamic-pituitary-adrenal (HPA) axis suppression with the potential for clinical glucocorticosteroid insufficiency. This may occur during treatment or upon withdrawal of the topical corticosteroid. In studies evaluating the potential for hypothalamic-pituitary-adrenal (HPA) axis suppression, using the Cosyntropin Stimulation Test, Clobetasol Propionate Topical Spray, 0.05% demonstrated rates of suppression that were comparable after 2 and 4 weeks of twice-daily use (19% and 15 to 20%, respectively), in adult patients with moderate to severe plaque psoriasis (≥ 20% BSA). In these studies, HPA axis suppression was defined as serum cortisol level ≤18 μg/dL 30-min post cosyntropin stimulation [ see Clinical Pharmacology (12)].

Because of the potential for systemic absorption, use of topical corticosteroids may require that patients be periodically evaluated for HPA axis suppression. Factors that predispose a patient using a topical corticosteroid to HPA axis suppression include the use of more potent steroids, use over large surface areas, use over prolonged periods, use under occlusion, use on an altered skin barrier, and use in patients with liver failure.

An ACTH stimulation test may be helpful in evaluating patients for HPA axis suppression. If HPA axis suppression is documented, an attempt should be made to gradually withdraw the drug, to reduce the frequency of application, or to substitute a less potent steroid. Manifestations of adrenal insufficiency may require supplemental systemic corticosteroids. Recovery of HPA axis function is generally prompt and complete upon discontinuation of topical corticosteroids.

Cushing's syndrome, hyperglycemia, and unmasking of latent diabetes mellitus can also result from systemic absorption of topical corticosteroids.

Use of more than one corticosteroid-containing product at the same time may increase the total systemic corticosteroid exposure. Pediatric patients may be more susceptible to systemic toxicity from use of topical corticosteroids. [ see Use in Specific Populations (8.4)]

5.2 Local Adverse Reactions with Topical Corticosteroids

The following additional local adverse reactions have been reported with topical corticosteroids. They may occur more frequently with the use of occlusive dressings and higher potency corticosteroids, including clobetasol propionate. These reactions are listed in an approximate decreasing order of occurrence: folliculitis, acneiform eruptions, hypopigmentation, perioral dermatitis, allergic contact dermatitis, secondary infection, striae and miliaria.

5.3 Allergic Contact Dermatitis

Allergic contact dermatitis to any component of topical corticosteroids is usually diagnosed by a failure to heal rather than a clinical exacerbation. Clinical diagnosis of allergic contact dermatitis can be confirmed by patch testing.

5.4 Concomitant Skin Infections

In the presence of dermatological infections, the use of an appropriate antifungal or antibacterial agent should be instituted. If a favorable response does not occur promptly, use of Clobetasol Propionate Topical Spray, 0.05% should be discontinued until the infection has been adequately controlled.

5.5 Flammable Contents

Clobetasol Propionate Topical Spray, 0.05% is flammable; keep away from heat or flame.

6. ADVERSE REACTIONS

6.1 Clinical Trials Experience

Because clinical trials are conducted under widely varying conditions, adverse reaction rates observed in the clinical trials of a drug cannot be directly compared to rates in the clinical trials of another drug and may not reflect the rates observed in practice.

In controlled, clinical trials with Clobetasol Propionate Topical Spray, 0.05%, the most common adverse reaction was burning at the site of application [40% of subjects treated with Clobetasol Propionate Topical Spray, 0.05% and 47% of subjects treated with Spray Vehicle]. Other commonly reported adverse reactions for Clobetasol Propionate Topical Spray, 0.05% and Spray Vehicle, respectively, are noted in Table 1.

Table 1 - Commonly Occurring Adverse Reactions (≥1% Incidence)
Adverse Reaction | Clobetasol Propionate Topical Spray, 0.05% (N=120) | Vehicle Spray (N=120)
System Organ Class
General disorders and administration site conditions | 50 (42%) | 56 (47%)
Application site burning | 48 (40%) | 56 (47%)
Application site dryness | 2 (2%) | 0 (0%)
Application site irritation | 1 (1%) | 0 (0%)
Application site pain | 1 (1%) | 2 (2%)
Application site pigmentation changes | 1 (1%) | 0 (0%)
Application site pruritus | 4 (3%) | 3 (3%)
Infections and infestations | 17 (14%) | 12 (10%)
Nasopharyngitis | 6 (5%) | 3 (3%)
Pharyngitis streptococcal | 1 (1%) | 0 (0%)
Upper respiratory tract infection | 10 (8%) | 2 (2%)
Skin and subcutaneous tissue disorders | 4 (3%) | 2 (2%)
Eczema asteatotic | 2 (2%) | 0 (0%)

Most local adverse reactions were rated as mild to moderate and they are not affected by age, race or gender.

Systemic absorption of topical corticosteroids has produced hypothalamic-pituitary-adrenal (HPA) axis suppression, manifestations of Cushing's syndrome, hyperglycemia, and glycosuria in some patients.

6.2 Postmarketing Experience

Because these reactions are reported voluntarily from a population of uncertain size, it is not always possible to reliably estimate their frequency or establish a causal relationship to drug exposure.

The following adverse reactions have been identified during post-approval use of Clobetasol Propionate Topical Spray, 0.05%.

Skin:Burning, pruritus, erythema, pain, irritation, rash, peeling, urticaria, and contact dermatitis.

8. USE IN SPECIFIC POPULATIONS

8.1 Pregnancy

Teratogenic Effects: Pregnancy Category C:

There are no adequate and well-controlled studies in pregnant women. Clobetasol Propionate Topical Spray, 0.05% should be used during pregnancy only if the potential benefit justifies the potential risk to the fetus.

Corticosteroids have been shown to be teratogenic in laboratory animals when administered systemically at relatively low dosage levels. Some corticosteroids have been shown to be teratogenic after dermal application to laboratory animals.

Clobetasol propionate is absorbed percutaneously, and when administered subcutaneously it was a significant teratogen in both the rabbit and the mouse.

Clobetasol propionate has greater teratogenic potential than steroids that are less potent.

The effect of clobetasol propionate on pregnancy outcome and development of offspring was studied in the rat. Clobetasol propionate was administered subcutaneously to female rats twice daily (0, 12.5, 25, and 50 μg/kg/day) from day 7 of presumed gestation through day 25 of lactation or day 24 presumed gestation for those rats that did not deliver a litter. The maternal NOEL for clobetasol propionate was less than 12.5 μg/kg/day due to reduced body weight gain and feed consumption during the gestation period. The reproductive NOEL in the dams was 25 μg/kg/day (ratio of animal dose to proposed human dose of 0.07 on a mg/m^2/day basis) based on prolonged delivery at a higher dose level. The no-observed-adverse-effect-level (NOAEL) for viability and growth in the offspring was 12.5 μg/kg/day (ratio of animal dose to proposed human dose of 0.03 on a mg/m^2/day basis) based on incidence of stillbirths, reductions in pup body weights on days 1 and 7 of lactation, increased pup mortality, increases in the incidence of umbilical hernia, and increases in the incidence of pups with cysts on the kidney at higher dose levels during the preweaning period. The weights of the epididymides and testes were significantly reduced at higher dosages. Despite these changes, there were no effects on the mating and fertility of the offspring.

8.3 Nursing Mothers

Systemically administered corticosteroids appear in human milk and could suppress growth, interfere with endogenous corticosteroid production, or cause other untoward effects. It is not known whether topical administration of corticosteroids could result in sufficient systemic absorption to produce detectable quantities in breast milk. Because many drugs are excreted in human milk, caution should be exercised when Clobetasol Propionate Topical Spray, 0.05% is administered to a nursing woman.

8.4 Pediatric Use

Use in patients under 18 years of age is not recommended, because safety has not been established and because numerically high rates of HPA axis suppression were seen with other clobetasol propionate topical formulations. Safety and effectiveness in pediatric patients treated with Clobetasol Propionate Topical Spray, 0.05% have not been established [ see Warnings and Precautions (5.1)].

Because of higher ratio of skin surface area to body mass, pediatric patients are at a greater risk than adults of HPA axis suppression and Cushing's syndrome when they are treated with topical corticosteroids. They are therefore also at greater risk of glucocorticosteroid insufficiency during and/or after withdrawal of treatment. Adverse effects including striae have been reported with inappropriate use of topical corticosteroids in infants and children.

HPA axis suppression, Cushing's syndrome, linear growth retardation, delayed weight gain, and intracranial hypertension have been reported in children receiving topical corticosteroids. Manifestations of adrenal suppression in children include low plasma cortisol levels and absence of response to ACTH stimulation. Manifestations of intracranial hypertension include bulging fontanelles, headaches, and bilateral papilledema.

8.5 Geriatric Use

Clinical studies of Clobetasol Propionate Topical Spray, 0.05% did not include sufficient numbers of patients aged 65 and over to adequately determine whether they respond differently than younger patients. In two randomized, vehicle controlled clinical trials, 21 of the 240 patients (9%) were over the age of 65. In general, dose selection for an elderly patient should be made with caution, usually starting at the low end of the dosing range, reflecting the greater frequency of decreased hepatic, renal or cardiac function, and of concomitant disease or other drug therapy.

10. OVERDOSAGE

Topically applied Clobetasol Propionate Topical Spray, 0.05% can be absorbed in sufficient amount to produce systemic effects [ see Warnings and Precautions (5.1)].

11. DESCRIPTION

Clobetasol Propionate Topical Spray, 0.05% contains clobetasol propionate, a synthetic fluorinated corticosteroid, for topical use. The corticosteroids constitute a class of primarily synthetic steroids used topically as anti-inflammatory and antipruritic agents. Clobetasol propionate is 21-chloro-9-fluoro-11β, 17-dihydroxy-16β -methylpregna-1,4-diene-3,20-dione 17-propionate, with the empirical formula C25H32ClFO5, and a molecular weight of 466.97 (CAS Registry Number 25122-46-7). The following is the chemical structure:

Clobetasol propionate is a white to almost white crystalline powder that is practically insoluble in water. Each gram of Clobetasol Propionate Topical Spray, 0.05% contains 0.5 mg of clobetasol propionate, in a clear, colorless liquid composed of alcohol, isopropyl myristate, sodium lauryl sulfate, and undecylenic acid.

12. CLINICAL PHARMACOLOGY

12.1 Mechanism of Action

Like other topical corticosteroids Clobetasol Propionate Topical Spray, 0.05% has anti-inflammatory, antipruritic, and vasoconstrictive properties. The mechanism of the anti-inflammatory activity of the topical steroids in general is unclear. However, corticosteroids are thought to act by induction of phospholipase A2inhibitory proteins, collectively called lipocortins. It is postulated that these proteins control the biosynthesis of potent mediators of inflammation such as prostaglandins and leukotrienes by inhibiting the release of their common precursor, arachidonic acid. Arachidonic acid is released from membrane phospholipids by phospholipase A2.

12.2 Pharmacodynamics

Vasoconstrictor Assay

Clobetasol Propionate Topical Spray, 0.05% is in the super-high range of potency as demonstrated in a vasoconstrictor study in healthy subjects when compared with other topical corticosteroids. However, similar blanching scores do not necessarily imply therapeutic equivalence.

Hypothalamic-Pituitary-Adrenal (HPA) Axis Suppression

The effect of Clobetasol Propionate Topical Spray, 0.05% on hypothalamic-pituitary-adrenal (HPA) axis function was investigated in adults in two studies. In the first study, patients with plaque psoriasis covering at least 20% of their body applied Clobetasol Propionate Topical Spray, 0.05% twice daily for up to 4 weeks. 15% (2 out of 13) of patients displayed adrenal suppression after 4 weeks of use based on the Cosyntropin Stimulation Test. The laboratory suppression was transient; all subjects returned to normal after cessation of drug use. In the second study, patients with plaque psoriasis covering at least 20% of their body applied Clobetasol Propionate Topical Spray, 0.05% twice daily for either 2 or 4 weeks. 19% (4 out of 21) of patients treated for 2 weeks and 20% (3 out of 15) of patients treated for 4 weeks displayed adrenal suppression at the end of treatment based on the Cosyntropin Stimulation Test. The laboratory suppression was transient; all subjects returned to normal after cessation of drug use. In these studies, HPA axis suppression was defined as serum cortisol level ≤ 18 μg/dL 30-min post cosyntropin (ACTH1-24) stimulation [ see Warnings and Precautions (5)].

12.3 Pharmacokinetics

The extent of percutaneous absorption of topical corticosteroids is determined by many factors, including the vehicle, the integrity of the epidermal barrier and occlusion.

Topical corticosteroids can be absorbed from normal intact skin. Inflammation and other disease processes in the skin may increase percutaneous absorption.

There are no human data regarding the distribution of corticosteroids to body organs following topical application. Nevertheless, once absorbed through the skin, topical corticosteroids are handled through metabolic pathways similar to systemically administered corticosteroids. They are metabolized, primarily in the liver, and are then excreted by the kidneys. In addition, some corticosteroids and their metabolites are also excreted in the bile.

13. NONCLINICAL TOXICOLOGY

13.1 Carcinogenesis, Mutagenesis, Impairment of Fertility

Clobetasol propionate was not carcinogenic to rats when topically applied for 2 years at concentrations up to 0.005% which corresponded to doses up to 11 μg/kg/day (ratio of animal dose to proposed human dose of 0.03 on a mg/m^2/day basis).

Clobetasol propionate at concentrations up to 0.001% did not increase the rate of formation of ultra violet light-induced skin tumors when topically applied to hairless mice 5 days per week for a period of 40 weeks. Clobetasol propionate was negative in the in vitromammalian chromosomal aberration test and in the in vivomammalian erythrocyte micronucleus test.

The effect of subcutaneously administered clobetasol propionate on fertility and general reproductive toxicity was studied in rats at doses of 0, 12.5, 25, and 50 μg/kg/day. Males were treated beginning 70 days before mating and females beginning 15 days before mating through day 7 of gestation. A dosage level of less than 12.5 μg/kg/day clobetasol propionate was considered to be the no-observed-effect-level (NOEL) for paternal and maternal general toxicity based on decreased weight gain and for male reproductive toxicity based on increased weights of the seminal vesicles with fluid. The female reproductive NOEL was 12.5 μg/kg/day (ratio of animal dose to proposed human dose of 0.03 on a mg/m^2/day basis) based on reduction in the numbers of estrous cycles during the pre-cohabitation period and an increase in the number of nonviable embryos at higher doses.

14. CLINICAL STUDIES

The efficacy of Clobetasol Propionate Topical Spray, 0.05% in psoriasis has been demonstrated in two randomized, vehicle controlled clinical trials, which were identical in design. The studies were conducted in patients aged 18 years and older with moderate to severe plaque psoriasis. Patients were treated twice daily for up to 4 weeks with either Clobetasol Propionate Topical Spray, 0.05% or vehicle spray.

Patients were evaluated on their Overall Disease Severity, a 5-point scale based on scaling, erythema, and plaque elevation that classified subjects as clear, almost clear, mild, moderate, or severe/very severe. Only patients classified as moderate or severe/very severe at baseline were enrolled in the studies. The median percent body surface area (BSA) at baseline was 6% for the two studies. The numbers of patients scored as clear or almost clear at Weeks 2 and 4 are presented in Table 2.

Table 2-Number of Patients Clear or Almost Clear on the Overall Disease Severity Scale at Weeks 2 & 4
 |  | Study 1 |  | Study 2
 |  | Clobetasol Propionate Topical Spray, 0.05% | Vehicle | Clobetasol Propionate Topical Spray, 0.05% | Vehicle
 |  | N=60 | N=60 | N=60 | N=60
Week 2 | Clear | 1 (2%) | 0 (0%) | 0 (0%) | 0 (0%)
 | Almost Clear | 32 (53%) | 1 (2%) | 28 (47%) | 0 (0%)
Week 4 | Clear | 15 (25%) | 0 (0%) | 18 (30%) | 0 (0%)
 | Almost Clear | 32 (53%) | 2 (3%) | 31 (52%) | 1 (2%)

16. HOW SUPPLIED/STORAGE AND HANDLING

Clobetasol Propionate Topical Spray, 0.05% is a clear, colorless liquid, supplied in a white HDPE bottle with a white polypropylene cap and white LDPE liner in the following sizes:

2 fl oz/59 mL NDC51672-1371-4

4.25 fl oz/125 mL NDC51672-1371-8

STORAGE AND HANDLING

Storage:Keep tightly closed. Store at 20° to 25°C (68° to 77°F)[see USP Controlled Room Temperature]. Do not freeze, refrigerate or store above 30°C. Spray is flammable; avoid heat, flame or smoking when using this product.

17. PATIENT COUNSELING INFORMATION

[See FDA-approved patient labeling (Patient Information)]

17.1 Information for Patients

Patients using topical corticosteroids should receive the following information and instructions:

- This medication is to be used as directed by the physician and should not be used longer than the prescribed time period.
- This medication should not be used for any disorder other than that for which it was prescribed.
- Do not use other corticosteroid-containing products while using Clobetasol Propionate Topical Spray, 0.05% unless directed by your physician.
- The treated skin area should not be bandaged, otherwise covered, or wrapped so as to be occlusive unless directed by the physician.
- Patients should wash their hands after applying the medication.
- Patients should report any signs of local or systemic adverse reactions to the physician.
- Patients should inform their physicians that they are using Clobetasol Propionate Topical Spray, 0.05% if surgery is contemplated.
- If you go to another doctor for illness, injury or surgery, tell that doctor you are using Clobetasol Propionate Topical Spray, 0.05%.
- This medication is for external use only. It should not be used on the face, underarms, or groin area. Also avoid contact with the eyes and lips.
- As with other corticosteroids, therapy should be discontinued when control is achieved. If no improvement is seen within 2 weeks, contact the physician.
- Patients should not use more than 50 g (59 mL or 2 fl.oz.) per week of Clobetasol Propionate Topical Spray, 0.05%.
- Do not use more than 26 sprays per application or 52 sprays per day.
- This medication is flammable; avoid heat, flame or smoking when applying this product.

17.2 Instructions to the Pharmacist:

1. Remove the spray pump from the wrapper
2. Remove and discard the cap from the bottle
3. Keeping the bottle vertical, insert the spray pump into the bottle and turn clockwise until well-fastened
4. Dispense the bottle with the spray pump inserted

Mfd. by: Taro Pharmaceuticals Inc., Brampton, Ontario, Canada L6T 1C1
Dist. by: Taro Pharmaceuticals U.S.A., Inc., Hawthorne, NY 10532

Issued: November 2015
PPK-8022-0
68

PATIENT INFORMATION Clobetasol Propionate (kloe bay' ta sol proe' pee oh nate) Topical Spray, 0.05%

Important: For use on skin only. Do not get Clobetasol Propionate Topical Spray near or in your eyes, mouth or vagina.

Read the Patient Information that comes with Clobetasol Propionate Topical Spray before you start using it and each time you get a refill. There may be new information. This information does not take the place of talking with your doctor about your medical condition or your treatment.

What is Clobetasol Propionate Topical Spray, 0.05%?

Clobetasol Propionate Topical Spray is a prescription corticosteroid medicine used to treat adults with moderate to severe plaque psoriasis that affects up to 20% of the body's skin surface. Clobetasol Propionate Topical Spray is for use on the skin only (topical).

- Clobetasol Propionate Topical Spray should only be used for the shortest amount of time needed to treat your plaque psoriasis.
- Do not use more than 26 sprays for each application or more than 52 sprays in 1 day.
- You should not apply more than 59 mL (2 fluid ounces) of Clobetasol Propionate Topical Spray to your skin in 1 week.

You should not use Clobetasol Propionate Topical Spray, 0.05%:

- on your face, underarms (armpits), or groin areas
- if you have thinning of the skin (atrophy) at the treatment site
- to treat rosacea or a rash around the mouth (perioral dermatitis)

It is not known if Clobetasol Propionate Topical Spray is safe and effective in children under 18 years of age. Clobetasol Propionate Topical Spray should not be used in children under 18 years of age.

What should I tell my doctor before using Clobetasol Propionate Topical Spray, 0.05%?

Before you use Clobetasol Propionate Topical Spray, tell your doctor if you:

- have a skin infection. You may need medicine to treat the skin infection before you use Clobetasol Propionate Topical Spray.
- plan to have surgery
- have any other medical conditions
- are pregnant or plan to become pregnant. It is not known if Clobetasol Propionate Topical Spray will harm your unborn baby.
- are breast-feeding or plan to breast-feed. It is not known if Clobetasol Propionate Topical Spray passes into your breast milk. Talk to your doctor about the best way to feed your baby if you use Clobetasol Propionate Topical Spray.

Tell your doctor about all the medicines you take,including prescription and non-prescription medicines, vitamins and herbal supplements. Especially tell your doctor if you take other corticosteroid medicines by mouth or use other products on your skin that contain corticosteroids. Ask your doctor or pharmacist if you are not sure.

Know the medicines you take. Keep a list of them to show your doctor and pharmacist when you get a new medicine.

How should I use Clobetasol Propionate Topical Spray, 0.05%?

- Use Clobetasol Propionate Topical Spray exactly as your doctor tells you to use it.
- Your doctor should tell you how much Clobetasol Propionate Topical Spray to use and where to apply it.
- Clobetasol Propionate Topical Spray is for use on skin only. Do not get Clobetasol Propionate Topical Spray near or in your eyes, mouth, or vagina.
- You should not use Clobetasol Propionate Topical Spray on your face, underarms (armpits), or groin areas.
- Apply Clobetasol Propionate Topical Spray 2 times each day.
- Apply only enough Clobetasol Propionate Topical Spray to cover the affected skin areas. Rub in gently and completely.
- Wash your hands after using Clobetasol Propionate Topical Spray.
- Throw away any unused Clobetasol Propionate Topical Spray.
- Do not bandage or cover your treated areas unless your doctor tells you to.
- Tell your doctor if your skin condition is not getting better after 2 weeks of using Clobetasol Propionate Topical Spray. Your doctor may tell you to apply Clobetasol Propionate Topical Spray to certain areas of your skin for up to 2 more weeks if needed. You should not use Clobetasol Propionate Topical Spray for more than 4 weeks unless your doctor tells you to. This can increase your risk of serious side effects.

See the " Instructions for Use" at the end of the Patient Information for detailed information about the right way to apply Clobetasol Propionate Topical Spray.

What should I avoid while using Clobetasol Propionate Topical Spray, 0.05%?

- Clobetasol Propionate Topical Spray is flammable.Avoid heat, flames or smoking while applying Clobetasol Propionate Topical Spray to your skin.

What are the possible side effects of Clobetasol Propionate Topical Spray, 0.05%?

- Clobetasol Propionate Topical Spray can pass through your skin.Too much Clobetasol Propionate Topical Spray passing through your skin can cause your adrenal glands to stop working. Your doctor may do blood tests to check how well your adrenal glands are working.

The most common side effects of Clobetasol Propionate Topical Spray include:

- burning at treated site
- upper respiratory tract infection
- runny nose
- sore throat
- dry, itchy, and reddened skin

If you go to another doctor for illness, injury or surgery, tell that doctor you are using Clobetasol Propionate Topical Spray.

Tell your doctor if you have any side effect that bothers you or that does not go away. These are not all the possible side effects of Clobetasol Propionate Topical Spray. For more information, ask your doctor or pharmacist.

Call your doctor for medical advice about side effects. You may report side effects to FDA at 1-800-FDA-1088.

You may also report side effects to Taro Pharmaceuticals U.S.A., Inc. at 1-866-923-4914.

How should I store Clobetasol Propionate Topical Spray, 0.05%?

- Store Clobetasol Propionate Topical Spray at room temperature between 68˚F to 77˚F (20˚C to 25˚C).
- Do not store Clobetasol Propionate Topical Spray above 86°F (30°C).
- Do not freeze or refrigerate Clobetasol Propionate Topical Spray.
- Keep the bottle of Clobetasol Propionate Topical Spray tightly closed.
- Keep away from heat or flame

Keep Clobetasol Propionate Topical Spray and all medicines out of the reach of children.

General information about Clobetasol Propionate Topical Spray, 0.05%.

Medicines are sometimes prescribed for purposes other than those listed in a Patient Information leaflet. Do not use Clobetasol Propionate Topical Spray for a condition for which it was not prescribed. Do not give Clobetasol Propionate Topical Spray to other people, even if they have the same symptoms that you have. It may harm them.

This Patient Information leaflet summarizes the most important information about Clobetasol Propionate Topical Spray. If you would like more information, talk with your doctor. You can ask your pharmacist or doctor for information about Clobetasol Propionate Topical Spray that is written for health professionals.

What are the ingredients in Clobetasol Propionate Topical Spray, 0.05%?

Activeingredient: clobetasol propionate

Inactiveingredients: alcohol, isopropyl myristate, sodium lauryl sulfate, and undecylenic acid

Instructions for Use Clobetasol Propionate (kloe bay' ta sol proe' pee oh nate) Topical Spray, 0.05%

Important: For use on skin only. Do not get Clobetasol Propionate Topical Spray near or in your mouth, eyes or vagina.

Read the Instructions for Use that comes with Clobetasol Propionate Topical Spray before you start using it and each time you get a refill. There may be new information. This information does not take the place of talking with your doctor about your medical condition or your treatment.

Parts of Clobetasol Propionate Topical Spray, 0.05% (See Figure A)

When you receive Clobetasol Propionate Topical Spray the Directional Spray Nozzle is in the "locked" position with the nozzle pointing downwards. (See Figure B)

How to apply Clobetasol Propionate Topical Spray, 0.05%:
Figure C | Step 1:To unlock the Directional Spray Nozzle, hold the Clobetasol Propionate Topical Spray bottle and sides of the Pump Top with one hand. Use your other hand to turn the Directional Spray Nozzle to either the right or the left (See Figure C). The spray will come out through the opening at the end of the Directional Spray Nozzle. |  | Figure D | Step 2:To apply Clobetasol Propionate Topical Spray, point the Directional Spray Nozzle to the affected area. To spray, push down on the Pump Top. Apply Clobetasol Propionate Topical Spray to the affected area as instructed by your doctor. (See Figure D)

Step 3:Spray only enough Clobetasol Propionate Topical Spray to cover the affected area, for example, the elbow (See Figure E). Rub in Clobetasol Propionate Topical Spray gently and completely.

- You should not apply Clobetasol Propionate Topical Spray to your face, underarms or groin. Avoid contact with your eyes and lips.
- To apply to your scalp, part your hair at the area where Clobetasol Propionate Topical Spray is to be applied. Spray directly on the affected area, and then rub in gently and completely. (See Figure F)
- Repeat Steps 2 and 3 to apply Clobetasol Propionate Topical spray to other affected areas as instructed by your doctor.

Figure G | Step 4:After applying Clobetasol Propionate Topical Spray, return the Directional Spray Nozzle to the "locked" position. (See Figure G) |  | Step 5:Wash your hands after applying Clobetasol Propionate Topical Spray.

This Patient Information and Instructions for Use have been approved by the U.S. Food and Drug Administration.

Mfd. by: Taro Pharmaceuticals Inc., Brampton, Ontario, Canada L6T 1C1
Dist. by: Taro Pharmaceuticals U.S.A., Inc.,Hawthorne, NY 10532
Issued: November 2015
PPK-8022-0
68

PRINCIPAL DISPLAY PANEL - 59 mL Bottle Carton

2 fl oz/59 mL

NDC 51672-1371-4

Clobetasol
Propionate
Topical Spray

0.05%

FOR TOPICAL USE ONLY

Keep this and all
medications out of the
reach of children.

Rx only

TARO